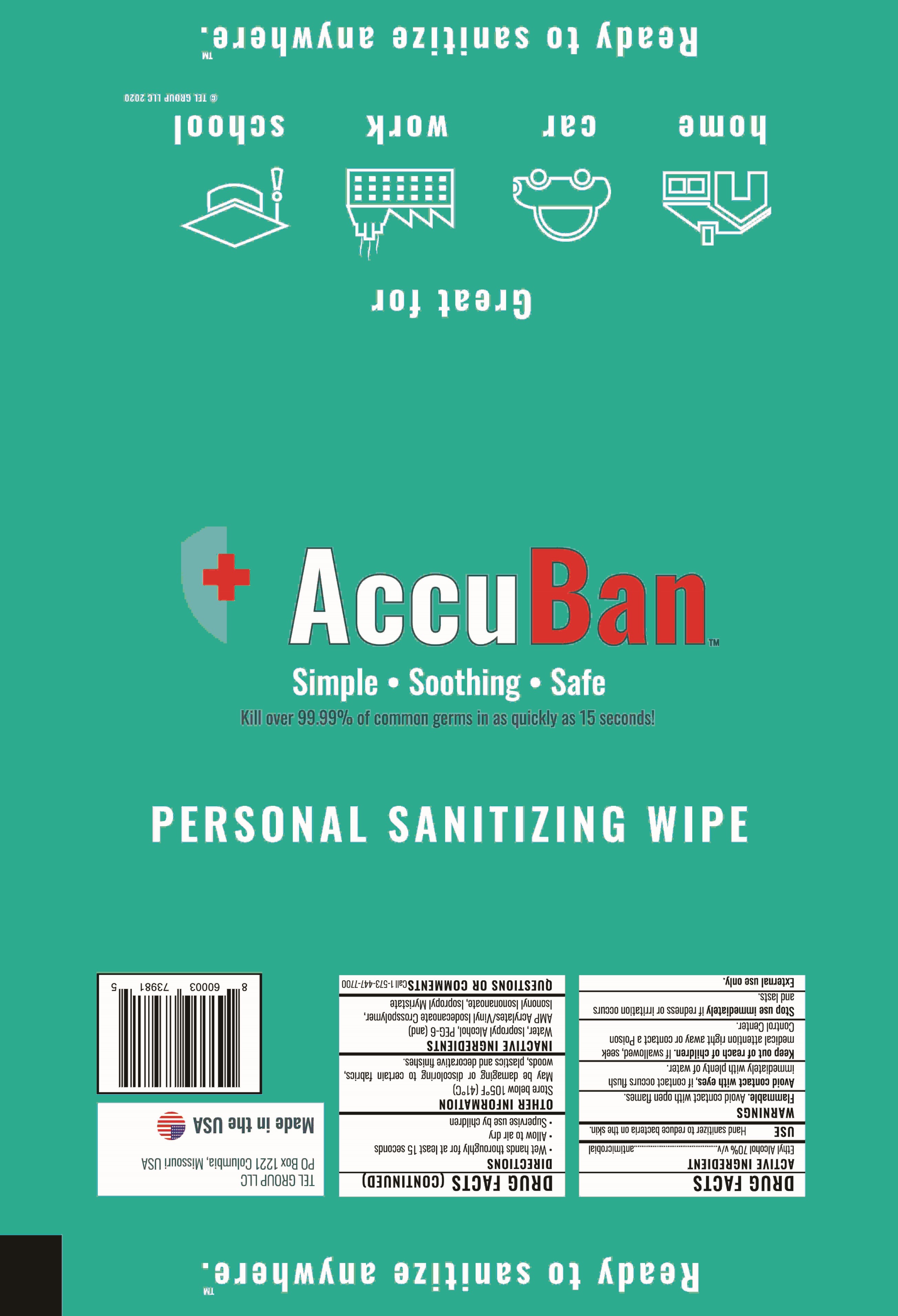 DRUG LABEL: AccuBan Wipes
NDC: 80620-210 | Form: SOLUTION
Manufacturer: TEL Group LLC
Category: otc | Type: HUMAN OTC DRUG LABEL
Date: 20201019

ACTIVE INGREDIENTS: ALCOHOL 0.70 1/1 1
INACTIVE INGREDIENTS: WATER; ISOPROPYL ALCOHOL

Drug Facts

Active Ingredient

Ethyl Alcohol 70% v/v ........ antimicrobial

Purpose

Antiseptic, Hand Sanitizer

Use

Hand Sanitizer to reduce bacteria on the skin.

Warnings

Flammable. Avoid contact with open flames.

WHEN USING

Avoid contact with eyes. If contact occurs flush immediately with plenty of water.

External use only

Stop use immediately if redness or irritation occurs and lasts.

Keep out of reach of children. If swallowed, seek medical attention right away or contact a Poison Control Center.

Directions

- Wet hands thoroughly for at lest 15 seconds
- Allow to air dry
- Supervise use by children

Other information

Store below 105F (41C)

May be damaging or discoloring to certain fabrics, wood, plastics and decorative finishes.

Inactive ingredients

Water, Isopropyl Alcohol, PEG-6 (and) AMP Acrylates/Vinyl Isodecanoate Crosspolymer, Isononyl Isononanoate, Isopropyl Myristate